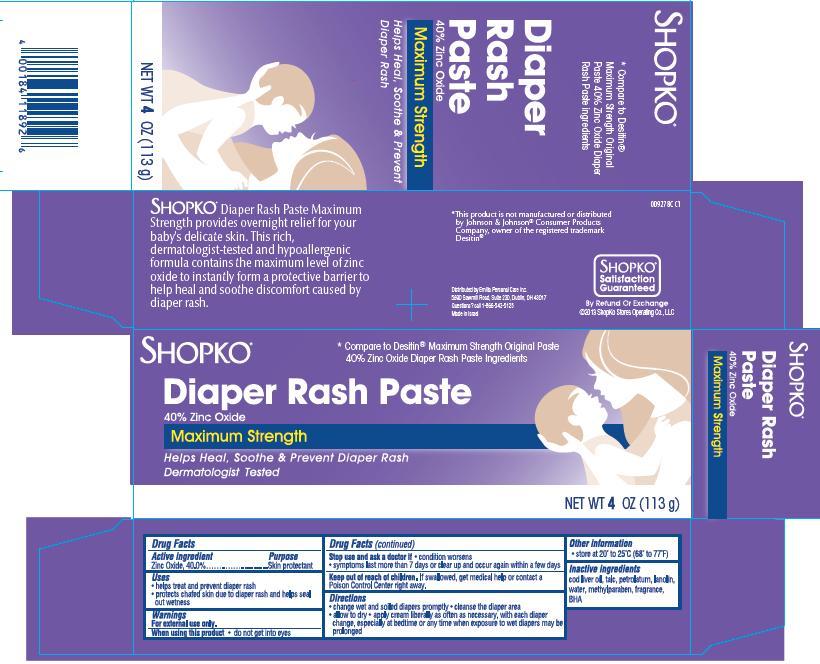 DRUG LABEL: Shopko Diaper Rash Maximum Strength
NDC: 37012-927 | Form: CREAM
Manufacturer: Shopko Stores Operating Co., LLC
Category: otc | Type: HUMAN OTC DRUG LABEL
Date: 20131203

ACTIVE INGREDIENTS: ZINC OXIDE 40 g/100 g
INACTIVE INGREDIENTS: COD LIVER OIL; TALC; PETROLATUM; LANOLIN; WATER; METHYLPARABEN; BUTYLATED HYDROXYANISOLE

SHOPKO® Diaper Rash Paste Maximum Strength

Active ingredient

Zinc Oxide........40.0%

Purpose

Skin Protectant

Uses

- helps treat and prevent diaper rash
- protects chafed skin due to diaper rash and helps seal out wetness

Warnings

For external use only.

When using this product

- do not get into eyes

Stop use and ask a doctor if

- condition worsens
- symptoms last more than 7 days or clear up and occur again within a few days

Keep Out of Reach of Children.

If swallowed, get medical help or contact a Poison Control Center right away.

Directions

- change wet and soiled diapers promptly
- cleanse the diaper area
- allow to dry
- apply cream liberally as often as necessary, with each diaper change, especially at bedtime or any time when exposure to wet diapers may be prolonged

Other Information

- store at 20º to 25ºC (68º to 77ºF)

Inactive ingredients

cod liver oil, talc, petrolatum, lanolin, water, methylparaben, fragrance, BHA

Package/Label Principal Display Panel

SHOPKO®

Diaper Rash Paste Maximum Strength

40% Zinc Oxide

Helps Heal, Soothe & Prevent Diaper Rash

Compare to Desitin® Maximum Strength Original Paste 40% Zinc Oxide Diaper Rash Paste Ingredients

NET WT 4 OZ (113 g)

SHOPKO® Diaper Rash Paste Maximum Strength provides overnight relief for your baby's delicate skin. This rich, dermatologist-tested and hypoallergenic formula contains the maximum level of zinc oxide to instantly form a protective barrier to help heal and soothe discomfort caused by diaper rash.

*This product is not manufactured or distributed by Johnson & Johnson® Consumer Products Company, owner of the registered trademark Desitin®

Distributed by Emilia Personal Care Inc.
5890 Sawmill Road, Suite 230, Dublin, OH 43017
Questions? Call 1-866-543-5125
Made in Israel
SHOPKO® Satisfaction Guaranteed
By Refund or Exchange
©2013 ShopKo Stores Operating Co., LLC
0D927 8C C1

Carton Label